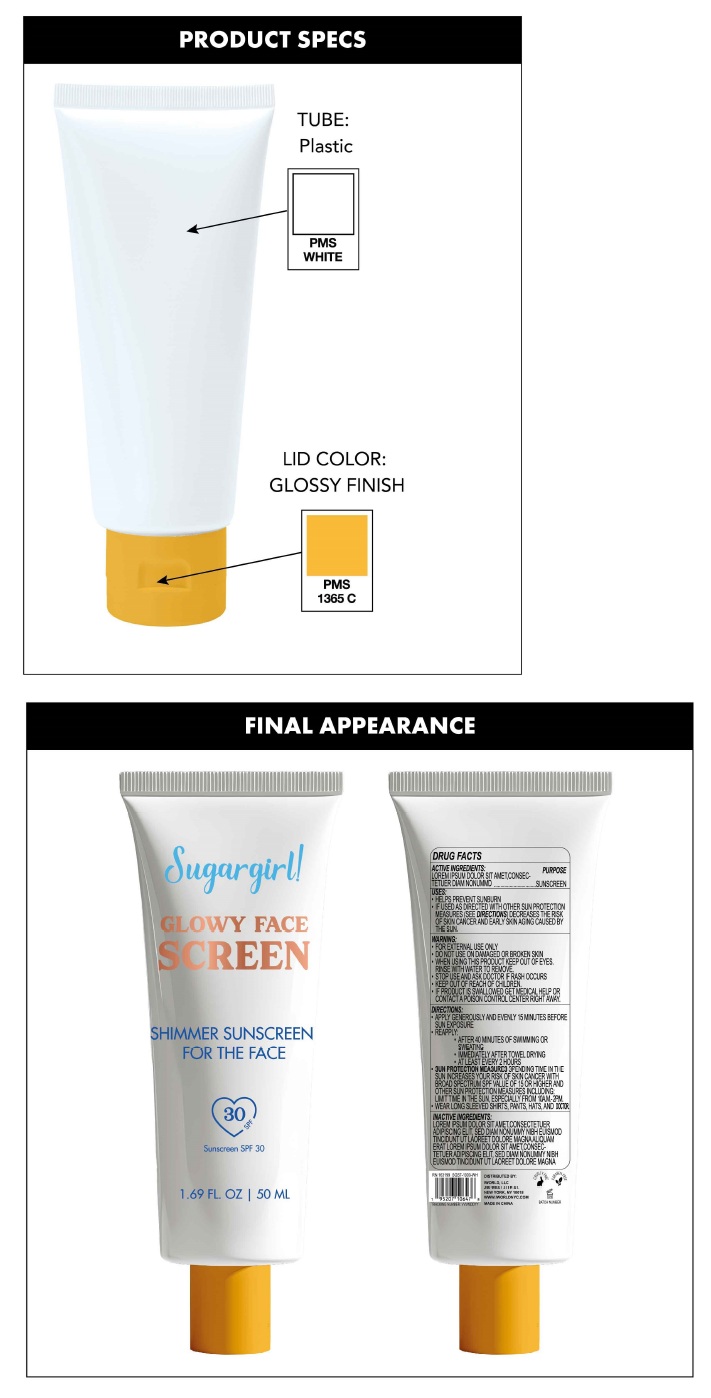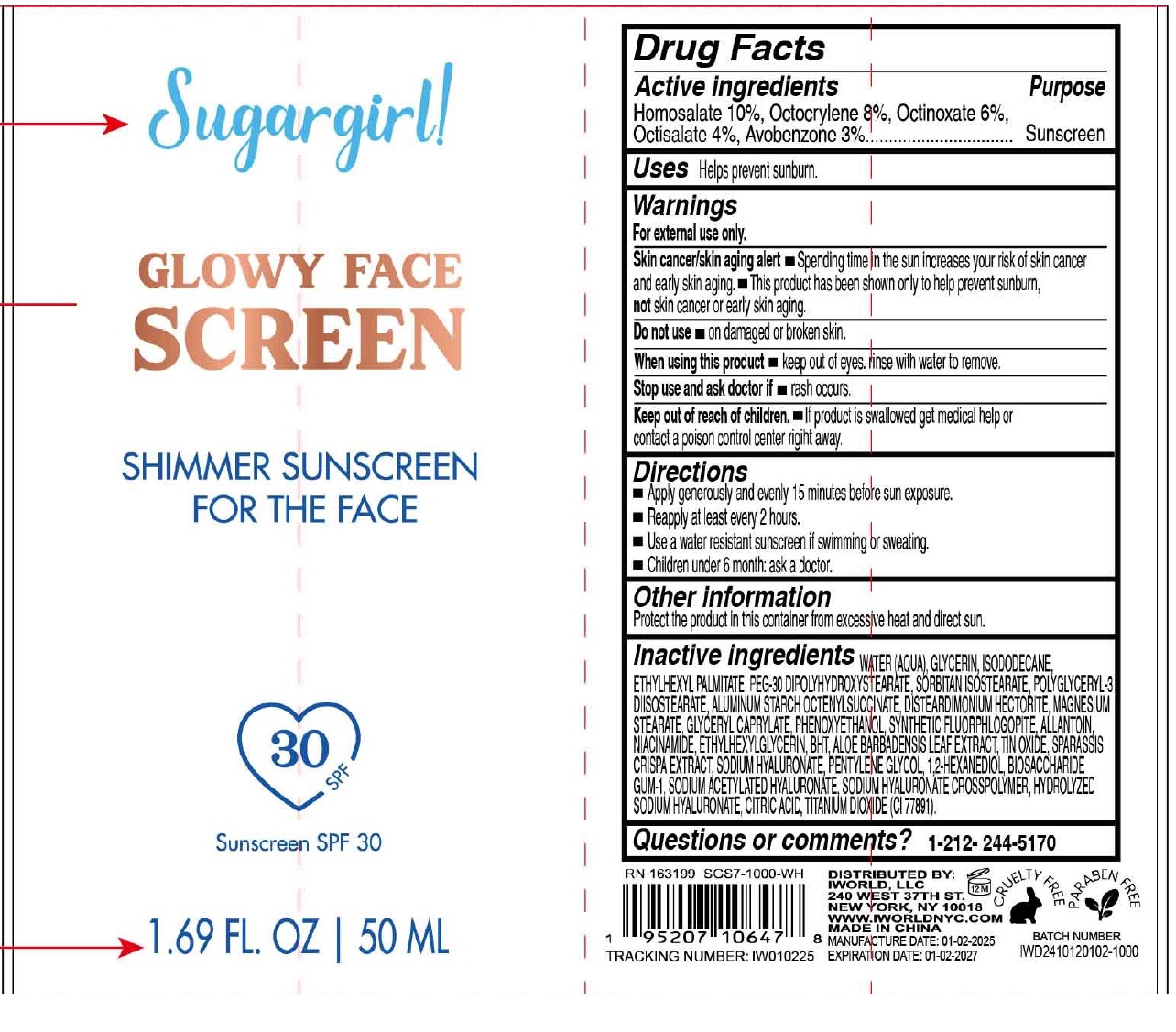 DRUG LABEL: Sugargirl Glowy Face Screen Shimmer Sunscreen SPF 30
NDC: 85179-003 | Form: LOTION
Manufacturer: I World LLC
Category: otc | Type: HUMAN OTC DRUG LABEL
Date: 20250120

ACTIVE INGREDIENTS: HOMOSALATE 100 mg/1 mL; OCTOCRYLENE 80 mg/1 mL; OCTINOXATE 60 mg/1 mL; OCTISALATE 40 mg/1 mL; AVOBENZONE 30 mg/1 mL
INACTIVE INGREDIENTS: WATER; GLYCERIN; ISODODECANE; ETHYLHEXYL PALMITATE; PEG-30 DIPOLYHYDROXYSTEARATE; SORBITAN ISOSTEARATE; POLYGLYCERYL-3 DIISOSTEARATE; ALUMINUM STARCH OCTENYLSUCCINATE; DISTEARDIMONIUM HECTORITE; MAGNESIUM STEARATE; GLYCERYL MONOCAPRYLATE; PHENOXYETHANOL; ALLANTOIN; NIACINAMIDE; ETHYLHEXYLGLYCERIN; BUTYLATED HYDROXYTOLUENE; ALOE VERA LEAF; STANNIC OXIDE; HYALURONATE SODIUM; PENTYLENE GLYCOL; 1,2-HEXANEDIOL; BIOSACCHARIDE GUM-1; SODIUM ACETYLATED HYALURONATE; CITRIC ACID MONOHYDRATE; TITANIUM DIOXIDE

Sugargirl Glowy Face Screen Shimmer Sunscreen SPF 30

Active ingredients

Homosalate 10%, Octocrylene 8%, Octinoxate 6%, Octisalate 4%, Avobenzone 3%

Purpose

Sunscreen

Uses

Helps prevent sunburn.

Warnings

For external use only.

Skin cancer/skin aging alert • Spending time in the sun increases your risk of skin cancer and early skin aging.

• This product has been shown only to help prevent sunburn, notskin cancer or early skin aging.

Do not use

- on damaged or broken skin.

When using this product

- Keep out of eyes. rinse with water to remove.

Stop use and ask doctor if

- rash occurs.

Keep out of reach of children.

- If product is swallowed get medical help or contact a Poison Control Center right away.

Directions

- Apply generously and evenly 15 minutes before sun exposure.
- Reapply at least every 2 hours.
- Use a water resistant sunscreen if swimming or sweating.
- Children under 6 month: ask a doctor.

Other information

Protect the product in this container from excessive heat and direct sun.

Inactive ingredients

WATER (AQUA), GLYCERIN, ISODODECANE, ETHYLHEXYL PALMITATE, PEG-30 DIPOLYHYDROXYSTEARATE, SORBITAN ISOSTEARATE, POLYGLYCERYL-3 DIISOSTEARATE, ALUMINUM STARCH OCTENYLSUCCINATE, DISTEARDIMONIUM HECTORITE, MAGNESIUM STEARATE, GLYCERYL CAPRYLATE, PHENOXYETHANOL, SYNTHETIC FLUORPHLOGOPITE, ALLANTOIN, NIACINAMIDE, ETHYLHEXYLGLYCERIN, BHT, ALOE BARBADENSIS LEAF EXTRACT, TIN OXIDE, SPARASSIS CRISPA EXTRACT, SODIUM HYALURONATE, PENTYLENE GLYCOL, 1,2-HEXANEDIOL, BIOSACCHARIDE GUM-1, SODIUM ACETYLATED HYALURONATE, SODIUM HYALURONATE CROSSPOLYMER, HYDROLYZED SODIUM HYALURONATE, CITRIC ACID, TITANIUM DIOXIDE (CI 77891).

Questions or comments?

1-212-244-5170